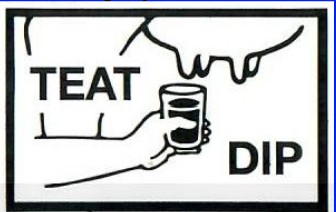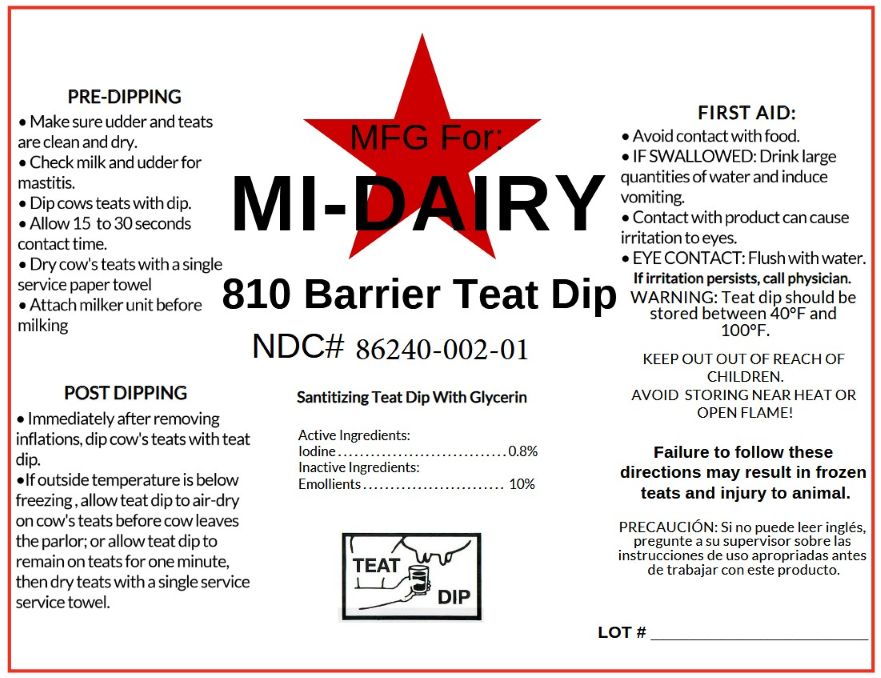 DRUG LABEL: 810 BarrierTeat Dip
NDC: 86240-002 | Form: SOLUTION
Manufacturer: Start City IBA, Inc.
Category: animal | Type: OTC ANIMAL DRUG LABEL
Date: 20250816

ACTIVE INGREDIENTS: IODINE 8 g/1 L
INACTIVE INGREDIENTS: SURFACTIN; GLYCERIN; SODIUM HYDROXIDE; WATER

MI-Dairy
810 Barrier Teat Dip

Active Ingredients:

Iodine............................0.8%

PURPOSE

Sanitizing Teat Dip With Glycerine

INDICATIONS AND USAGE

PRE-DIPPING

- Make sure udder and teats are clean and dry.
- Check milk and udder for mastitis.
- Dip or spray cows teats with dip.
- Allow 15 to 30 seconds contact time.
- Dry cow's teats with a single service paper towel before milking.
- Attach milker unit before milking.

POST DIPPING

- Immediately after removing inflations, dip or spray cow's teats with teat dip.
- If outside temperature is below freezing, allow teat dip to air-dry on cow's teats before cow leaves the parlor; or allow teat dip to remain on teats for one minute, then dry teats with a single service towel.

Failure to follow these directions may result in frozen teats and injury to animal.

FIRST AID

Avoid contact with food.

IF SWALLOWED: Drink large quantities of water and induce vomiting.

Contact with product can cause irritation to eyes.

FOR EYES: Flush with cool water for at least 15 minutes and obtain prompt medical attention. If irritation persists, call physician.

WARNINGS

WARNING: Teat dip should be stored between 40°F and 100°F.

KEEP OUT OF REACH OF CHILDREN

AVOID STORING NEAR HEAT OR OPEN FLAME!

INACTIVE INGREDIENT

Active Ingredients

Iodine..............................0.8%

Inactive ingredients:

Emollients.........................10%

PACKAGE LABEL

Mfg for MI-DAIRY